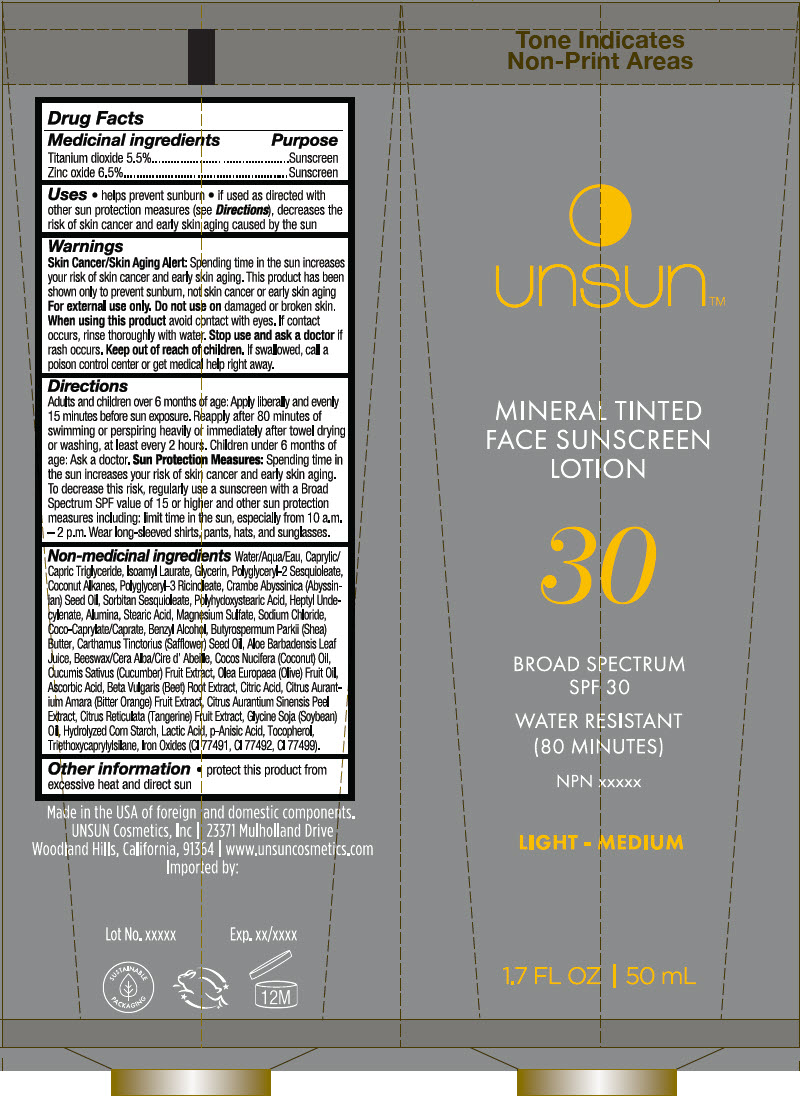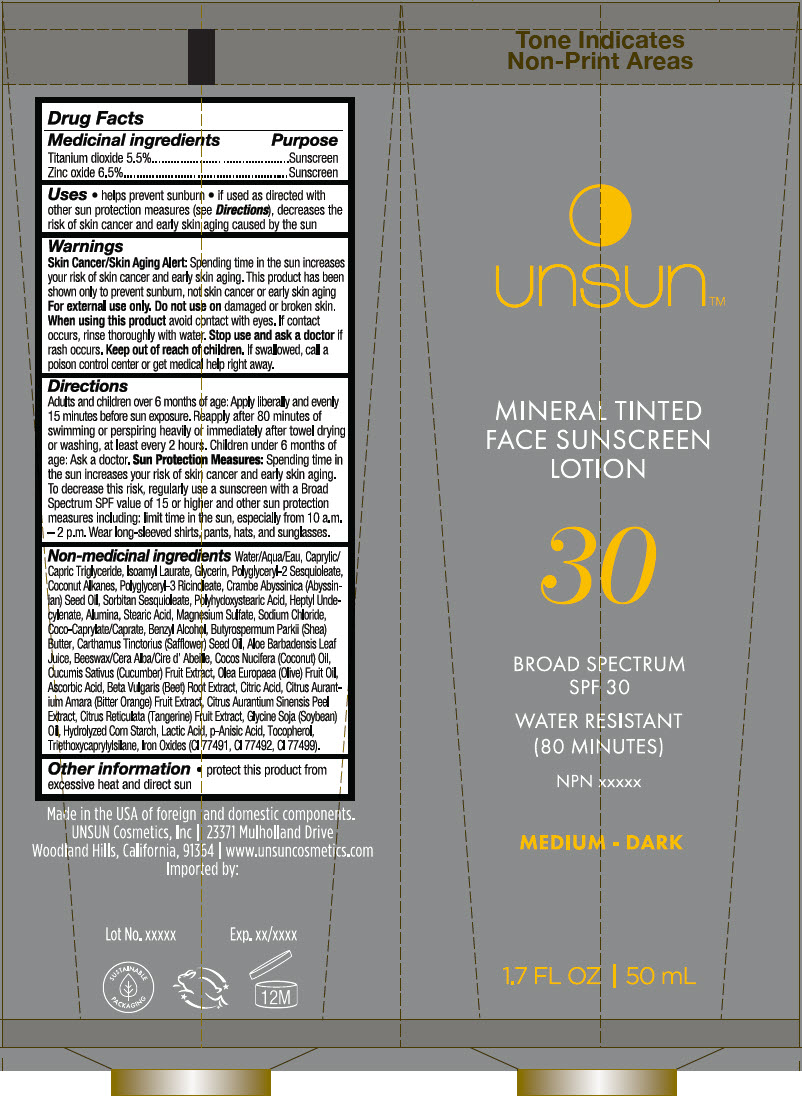 DRUG LABEL: Mineral Tinted Face Sunscreen SPF 30 - Light/ Medium
NDC: 73455-011 | Form: CREAM
Manufacturer: Unsun Cosmetics
Category: otc | Type: HUMAN OTC DRUG LABEL
Date: 20220324

ACTIVE INGREDIENTS: ZINC OXIDE 0.065 g/1 mL; Titanium Dioxide 0.055 g/1 mL
INACTIVE INGREDIENTS: water; COCONUT ALKANES; POLYGLYCERYL-3 RICINOLEATE; COCOYL CAPRYLOCAPRATE; CRAMBE HISPANICA SUBSP. ABYSSINICA SEED OIL; Sorbitan Sesquioleate; Heptyl Undecylenate

Mineral Tinted Face Sunscreen SPF 30

Drug Facts

ACTIVE INGREDIENT

Medicinal ingredients | Purpose
Titanium dioxide 5.5% | Sunscreen
Zinc oxide 6.5% | Sunscreen

Uses

- helps prevent sunburn
- if used as directed with other sun protection measures (see Directions), decreases the risk of skin cancer and early skin aging caused by the sun

Warnings

Skin Cancer/Skin Aging Alert

Spending time in the sun increases your risk of skin cancer and early skin aging. This product has been shown only to prevent sunburn, not skin cancer or early skin aging For external use only. Do not use on damaged or broken skin. When using this product avoid contact with eyes. If contact occurs, rinse thoroughly with water. Stop use and ask a doctor if rash occurs.

Keep out of reach of children. If swallowed, call a poison control center or get medical help right away.

Directions

Adults and children over 6 months of age: Apply liberally and evenly 15 minutes before sun exposure. Reapply after 80 minutes of swimming or perspiring heavily or immediately after towel drying or washing, at least every 2 hours. Children under 6 months of age: Ask a doctor. Sun Protection Measures: Spending time in the sun increases your risk of skin cancer and early skin aging. To decrease this risk, regularly use a sunscreen with a Broad Spectrum SPF value of 15 or higher and other sun protection measures including: limit time in the sun, especially from 10 a.m.– 2 p.m. Wear long-sleeved shirts, pants, hats, and sunglasses.

Non-medicinal ingredients

Water/Aqua/Eau, Caprylic/Capric Triglyceride, Isoamyl Laurate, Glycerin, Polyglyceryl-2 Sesquioleate, Coconut Alkanes, Polyglyceryl-3 Ricinoleate, Crambe Abyssinica (Abyssinian) Seed Oil, Sorbitan Sesquioleate, Polyhydroxystearic Acid, Heptyl Undecylenate, Alumina, Stearic Acid, Magnesium Sulfate, Sodium Chloride, Coco-Caprylate/Caprate, Benzyl Alcohol, Butyrospermum Parkii (Shea) Butter, Carthamus Tinctorius (Safflower) Seed Oil, Aloe Barbadensis Leaf Juice, Beeswax/Cera Alba/Cire d' Abeille, Cocos Nucifera (Coconut) Oil, Cucumis Sativus (Cucumber) Fruit Extract, Olea Europaea (Olive) Fruit Oil, Ascorbic Acid, Beta Vulgaris (Beet) Root Extract, Citric Acid, Citrus Aurantium Amara (Bitter Orange) Fruit Extract, Citrus Aurantium Sinensis Peel Extract, Citrus Reticulata (Tangerine) Fruit Extract, Glycine Soja (Soybean) Oil, Hydrolyzed Corn Starch, Lactic Acid, p-Anisic Acid, Tocopherol, Triethoxycaprylylsilane, Iron Oxides (CI 77491, CI 77492, CI 77499).

Other information

- protect this product from excessive heat and direct sun

PRINCIPAL DISPLAY PANEL - 50 mL Tube Label - Light Medium

unsun™

MINERAL TINTED
FACE SUNSCREEN
LOTION

30

BROAD SPECTRUM
SPF 30

WATER RESISTANT
(80 MINUTES)

NPN xxxxx

LIGHT - MEDIUM

1.7 FL OZ | 50 mL

PRINCIPAL DISPLAY PANEL - 50 mL Tube Label - Medium Dark

unsun™

MINERAL TINTED
FACE SUNSCREEN
LOTION

30

BROAD SPECTRUM
SPF 30

WATER RESISTANT
(80 MINUTES)

NPN xxxxx

MEDIUM - DARK

1.7 FL OZ | 50 mL